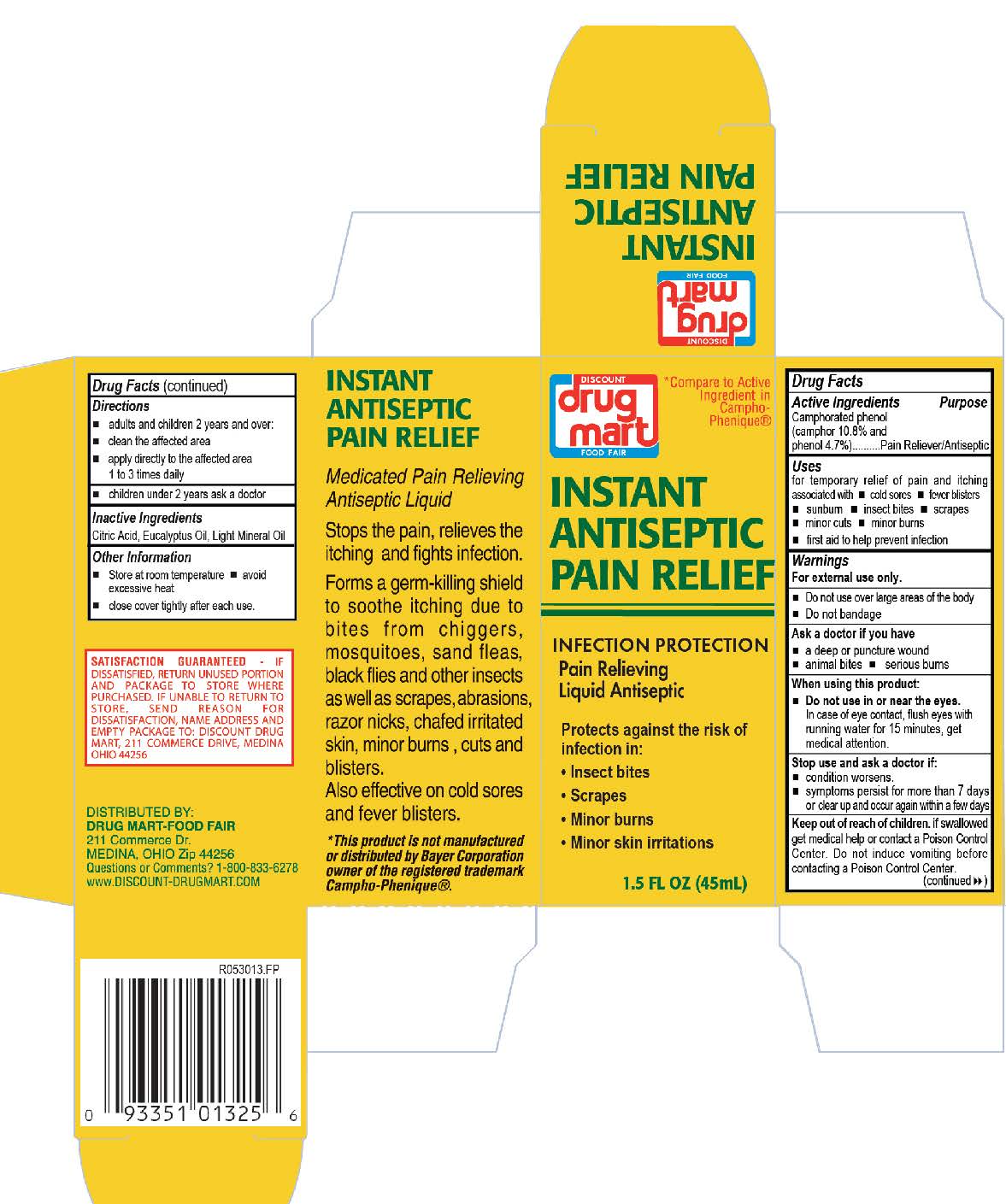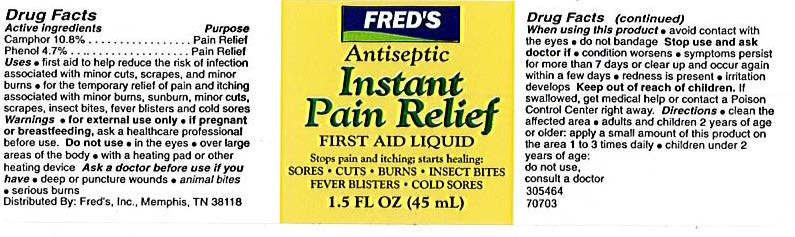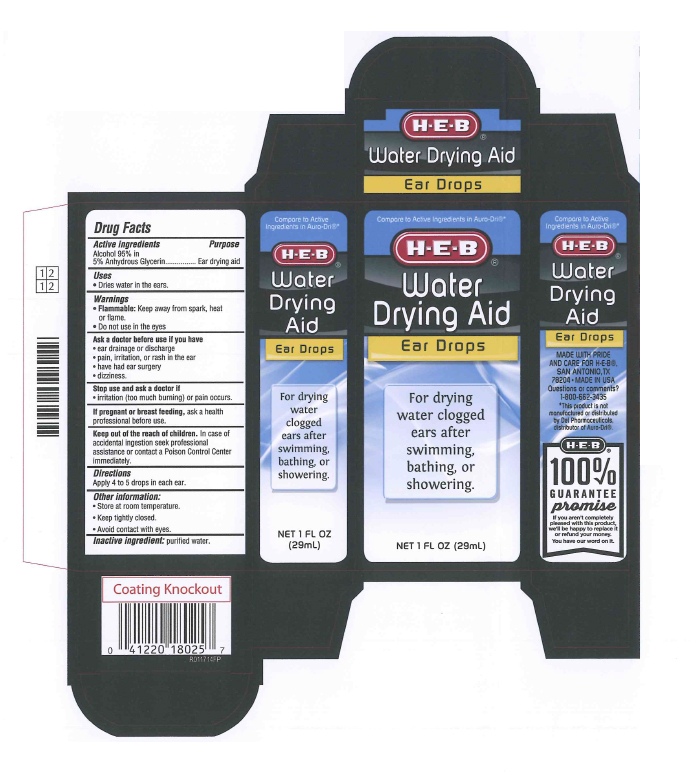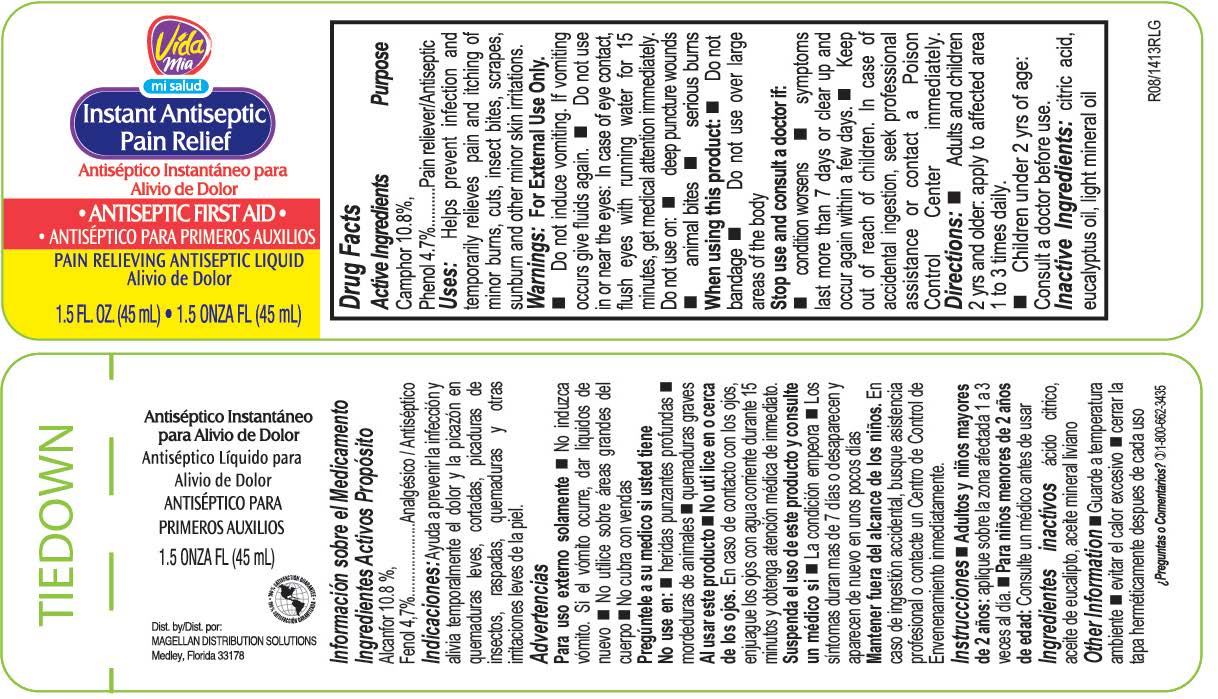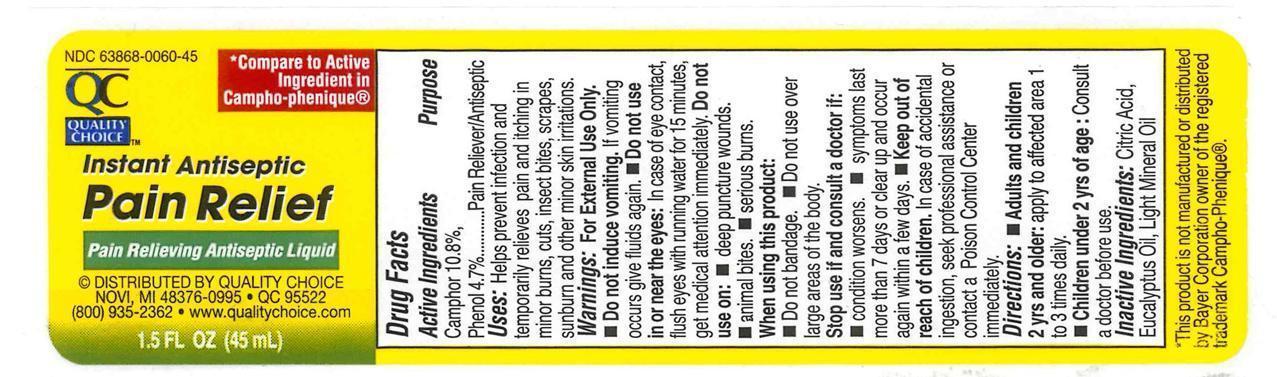 DRUG LABEL: Antiseptic Instant Pain Relief
NDC: 82645-902 | Form: LIQUID
Manufacturer: Pharma Nobis, LLC
Category: otc | Type: HUMAN OTC DRUG LABEL
Date: 20231222

ACTIVE INGREDIENTS: CAMPHOR (NATURAL) 108 mg/1 mL; PHENOL 47 mg/1 mL
INACTIVE INGREDIENTS: EUCALYPTUS OIL; LIGHT MINERAL OIL; ANHYDROUS CITRIC ACID

Private Label Antiseptic Instant Pain Relief

Drug Facts

Active Ingredients

Camphor 10.8%, Phenol 4.7 %

Purpose

Pain Reliever, Antiseptic

Uses:

Helps prevent infection and temporarily relieves pain and itching in minor burns, cuts, insect bites, scrapes, sunburn and other minor skin irritations.

Warnings:

For External Use Only. Do not induce vomiting. If vomiting occurs give fluids again. Do not use in or near the eyes: In case of eye contact, flush eyes with running water for 15 minutes, get medical attention immediately. Do not use on: deep punture wounds, animal bites, serious burns.

When using this product:

Do not bandage. Do not use over large areas of the body.

Stop use and consult a doctor if:

Condition worsens. Symptoms last more than 7 days or clear up and occur again in a few days.

Keep out of the reach of children.

In case of accidental ingestion, seek professional assistance or contact a Poison Control Center immediately.

Directions:

Adult and children 2 yrs and older: apply to affected area 1 to 3 times daily.

Children under 2 yrs of age: Consult a doctor before use.

Inactive ingredients:

Citric acid, Eucalyptus Oil, Light Mineral Oil